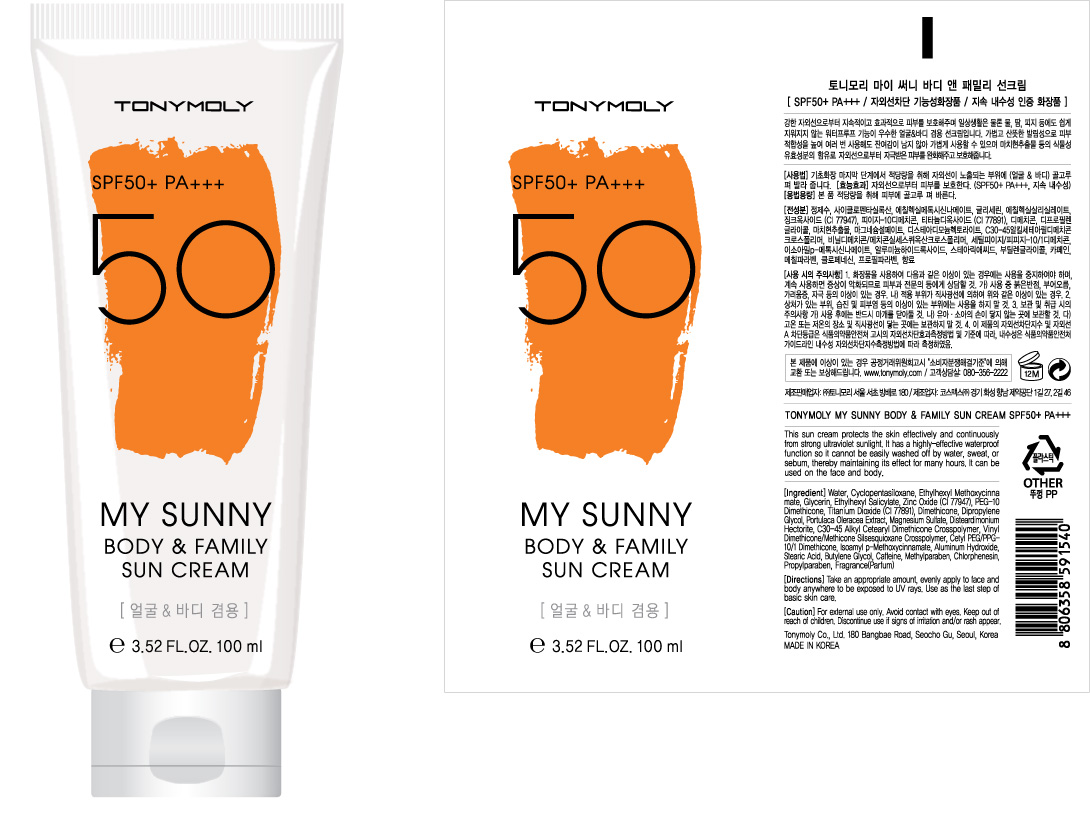 DRUG LABEL: TONYMOLY My Sunny Body and Family Sun Cream
NDC: 59078-121 | Form: CREAM
Manufacturer: Tonymoly Co., Ltd.
Category: otc | Type: HUMAN OTC DRUG LABEL
Date: 20160204

ACTIVE INGREDIENTS: GLYCERIN 6295 mg/100 mL; ZINC OXIDE 27489 mg/100 mL
INACTIVE INGREDIENTS: WATER; ALUMINUM HYDROXIDE; METHYLPARABEN; GLYCERYL CAPRYLATE; MAGNESIUM SULFATE; CHLORPHENESIN; CAFFEINE; DISTEARDIMONIUM HECTORITE; STEARIC ACID; PROPYLPARABEN; CYCLOMETHICONE 5; OCTISALATE; AMILOXATE; BUTYLENE GLYCOL; PORTULACA OLERACEA WHOLE

Active Ingredients

Dimethicone 2.10%, Dipropylene Glycol 2.00%, Ethylhexyl Methoxycinnamate 7.50%, Glycerin 5.00%, Titanium Dioxide 2.90%, Zinc Oxide 4.90%

Purpose

Sunscreen

Use

This sun cream protects the skin effectively and continuously from strong ultraviolet sunlight. It has a highly-effective waterproof function so it cannot be easily washed off by water, sweat, or sebum, thereby maintaining its effect for many hours. It can be used on the face and body.

Caution

For external use only. Avoid contact with eyes. Keep out of reach of children. Discontinue use if signs of irritation and/or rash appear.

Keep out of reach of children

Directions

Take an appropriate amount, evenly apply to face and body anywhere to be exposed to UV rays. Use as the last step of basic skin care.

Inactive Ingredients

Water, Cyclopentasiloxane, Ethylhexyl Salicylate, PEG-10 Dimethicone, Magnesium Sulfate, Disteardimonium Hectorite, C30-45 Alkyl Cetearyl Dimethicone Crosspolymer, Vinyl Dimethicone/Methicone Silsesquioxane Crosspolymer, Cetyl PEG/PPG-10/1 Dimethicone, Isoamyl p-Methoxycinnamate, Aluminum Hydroxide, Stearic Acid, Methylparaben, Chlorphenesin, Fragrance(Parfum), Caffeine, Butylene Glycol, Propylparaben, Portulaca Oleracea Extract